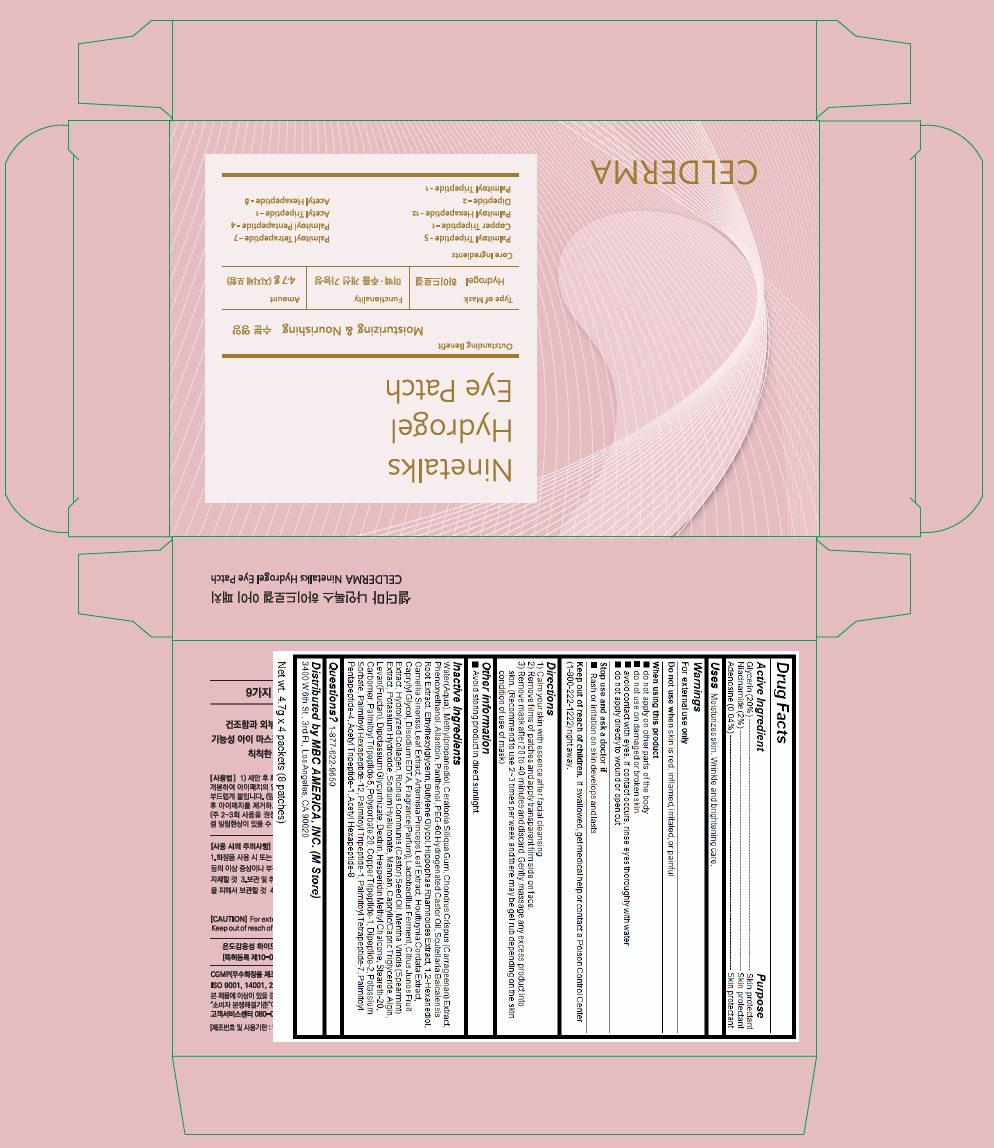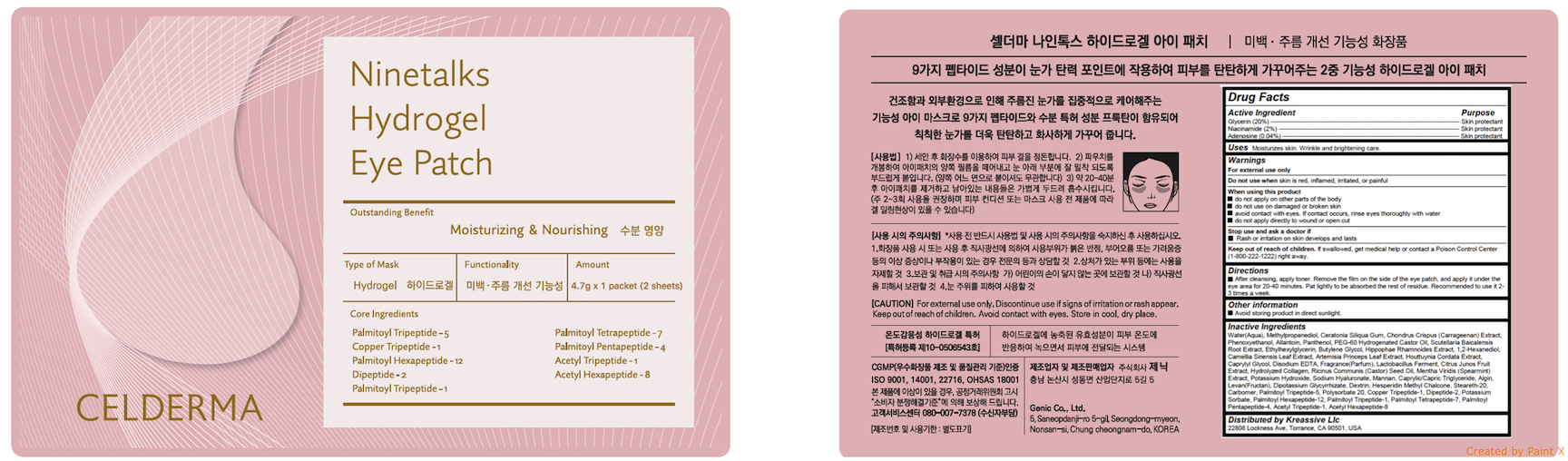 DRUG LABEL: CELDERMA Ninetalks Hydrogel Eye Patch Box
NDC: 72044-105 | Form: PATCH
Manufacturer: GENIC CO., LTD
Category: otc | Type: HUMAN OTC DRUG LABEL
Date: 20191231

ACTIVE INGREDIENTS: GLYCERIN 0.94 g/4.7 g; NIACINAMIDE 0.094 g/4.7 g; ADENOSINE 0.00188 g/4.7 g
INACTIVE INGREDIENTS: LOCUST BEAN GUM; METHYLPROPANEDIOL; PHENOXYETHANOL; ALLANTOIN; CHONDRUS CRISPUS CARRAGEENAN; WATER

CELDERMA Ninetalks Hydrogel Eye Patch

Active ingredients

Glycerin (20%)

Niacinamide (2%)

Adenosine (0.04%)

Purpose

skin protectant

Uses

Moisturizes skin. Wrinkle and brightening care.

Warnings

For external use only

Do not use when skin is red, inflamed, irritated, or painful

When using this product

- do not apply on other parts of the body
- do not use on damaged or broken skin
- avoid contact with eyes. If contact occurs, rinse eyes thoroughly with water
- do not apply directly to wound or open cut

Stop use and ask a doctor if

- Rash or irritation on skin develops and lasts

Keep out of reach of children

If swallowed, get medical help or contact a Poison Control Center (1-800-222-1222) right away.

Directions

After cleansing, apply toner. Remove the film on the side of the eye patch, and apply it under the eye area for 20-40 minutes. Pat lightly to be absorbed the rest of residue. Recommended to use it 2-3 times a week.

Inactive ingredients

Water(Aqua), Methylpropanediol, Ceratonia Siliqua Gum, Chondrus Crispus (Carrageenan) Extract, Phenoxyethanol, Allantoin, Panthenol, PEG-60 Hydrogenated Castor Oil, Scutellaria Baicalensis Root Extract, Ethylhexylglycerin, Butylene Glycol, Hippophae Rhamnoides Extract, 1,2-Hexanediol, Camellia Sinensis Leaf Extract, Artemisia Princeps Leaf Extract, Houttuynia Cordata Extract, Caprylyl Glycol, Disodium EDTA, Fragrance(Parfum), Lactobacillus Ferment, Citrus Junos Fruit Extract, Hydrolyzed Collagen, Ricinus Communis (Castor) Seed Oil, Mentha Viridis (Spearmint) Extract, Potassium Hydroxide, Sodium Hyaluronate, Mannan, Caprylic/Capric Triglyceride, Algin, Levan(Fructan), Dipotassium Glycyrrhizate, Dextrin, Hesperidin Methyl Chalcone, Steareth-20, Carbomer, Palmitoyl Tripeptide-5, Polysorbate 20, Copper Tripeptide-1, Dipeptide-2, Potassium Sorbate, Palmitoyl Hexapeptide-12, Palmitoyl Tripeptide-1, Palmitoyl Tetrapeptide-7, Palmitoyl Pentapeptide-4, Acetyl Tripeptide-1, Acetyl Hexapeptide-8